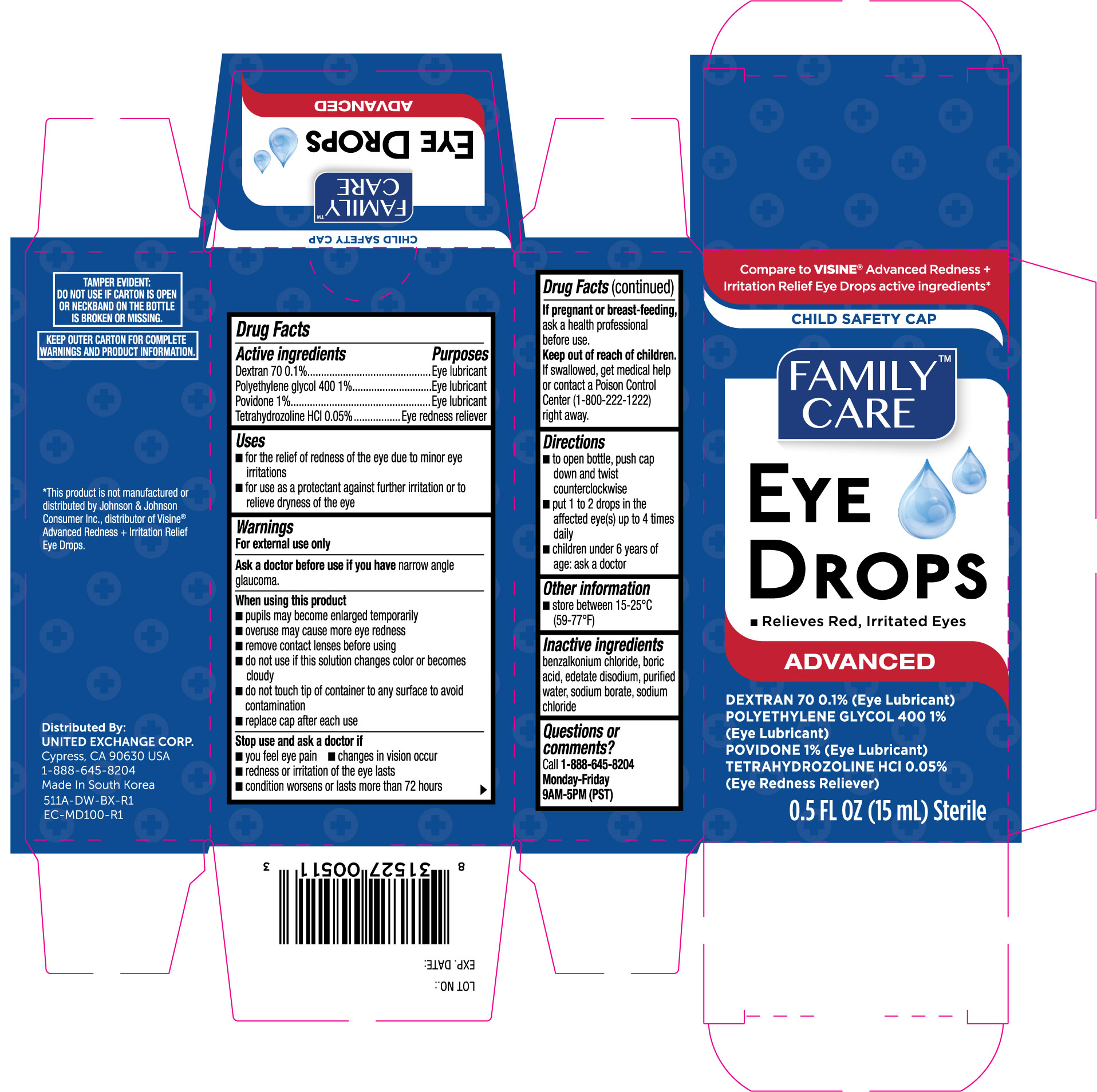 DRUG LABEL: Family Care Advanced Formula Eye
NDC: 65923-511 | Form: SOLUTION/ DROPS
Manufacturer: United Exchange Corp
Category: otc | Type: HUMAN OTC DRUG LABEL
Date: 20251029

ACTIVE INGREDIENTS: TETRAHYDROZOLINE HYDROCHLORIDE 0.5 mg/1 mL; DEXTRAN 70 1 mg/1 mL; POLYETHYLENE GLYCOL 400 10 mg/1 mL; POVIDONE 10 mg/1 mL
INACTIVE INGREDIENTS: BENZALKONIUM CHLORIDE; BORIC ACID; EDETATE DISODIUM; WATER; SODIUM CHLORIDE; SODIUM BORATE

Family Care Eye Drops Advanced Formula 0.5oz 511A (2020)

Active ingredients Purpose

Tetrahydrozoline HCl 0.05%.............................................................Redness reliever

Dextran 70 0.1%............................................................................Lubricant

Polyethylene glycol 400 1%.............................................................Lubricant

Povidone 1%.................................................................................Lubricant

Uses

- for the relief of redness of the eyes due to minor eye irritations
- for use as a protectant against further irritation or to relieve dryness of the eye

Warnings

For external use only

Ask a doctor before use if you have narrow angle glaucoma.

When using this product

- pupils may become enlarged temporarily
- overuse may cause more eye redness
- remove contact lenses before using
- do not use if this solution changes color or becomes cloudy
- to avoid contamination, do not touch tip of container to any surface
- replace cap after each use

Stop use and ask a doctor if

- you feel eye pain
- changes in vision occur
- redness or irritation of the eye persists
- condition worsens or lasts more than 72 hours

PREGNANCY OR BREAST FEEDING

If pregnant or breast-feeding, ask a health professional before use.

KEEP OUT OF REACH OF CHILDREN

Keep out of the reach of children. If swallowed, get medical help or contact a Poison Control Center right away.

Directions

- to open bottle, push cap down and twist counter-clockwise
- put 1 to 2 drops in the affected eye(s) up to 4 times daily
- children under 6 years of age: ask a doctor

Other information

- store at 15° to 25°C (59° to 77°F)

INACTIVE INGREDIENT

Inactive ingredients: benzalkonium chloride, boric acid, edetate disodium, purified water, sodium chloride, and sodium borate

DOSAGE AND ADMINISTRATION

Distributed by:

United Exchange Corp.

Cypress, CA 90630 USA

Made in South Korea